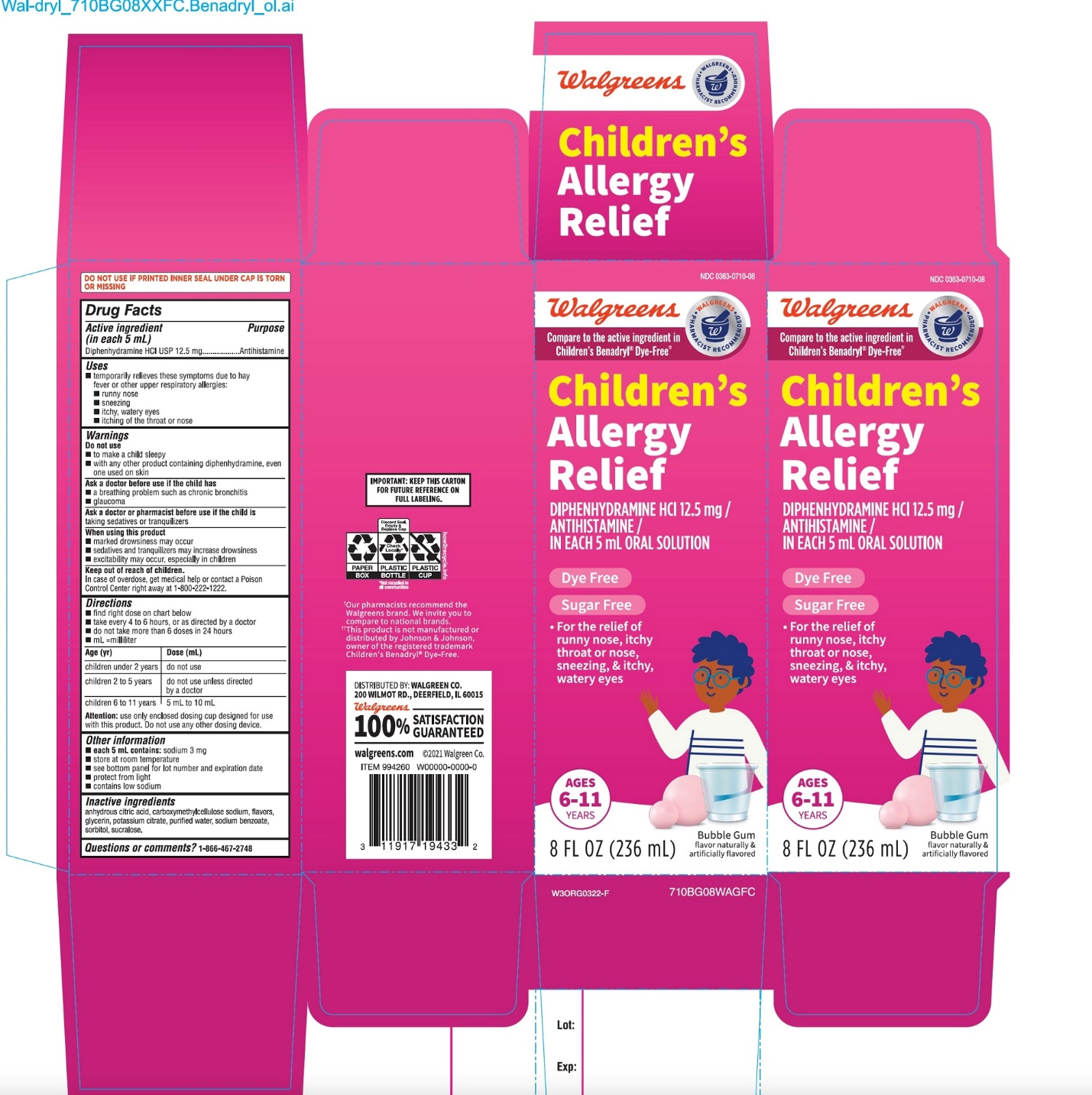 DRUG LABEL: childrens Allergy Dye Free Wal Dryl
NDC: 0363-0710 | Form: LIQUID
Manufacturer: WALGREEN CO.
Category: otc | Type: HUMAN OTC DRUG LABEL
Date: 20251125

ACTIVE INGREDIENTS: DIPHENHYDRAMINE HYDROCHLORIDE 12.5 mg/5 mL
INACTIVE INGREDIENTS: CARBOXYMETHYLCELLULOSE SODIUM, UNSPECIFIED; ANHYDROUS CITRIC ACID; GLYCERIN; POTASSIUM CITRATE; WATER; SODIUM BENZOATE; SORBITOL; SUCRALOSE

children’s ALLERGY Dye-Free Wal-Dryl®Diphenhydramine HCl Antihistamine 12.5 mg /5 mL ORAL SOLUTION

Drug Facts

Active ingredient (in each 5 mL)

Diphenhydramine HCl USP 12.5 mg

Purpose

Antihistamine

Uses

- temporarily relieves these symptoms due to hay fever or other upper respiratory allergies:
  - runny nose
  - sneezing
  - itchy, watery eyes
  - itching of the throat or nose

Warnings

Do not use

- to make a child sleepy
- with any other product containing diphenhydramine, even one used on skin

Ask a doctor before use if the child has

- a breathing problem such as chronic bronchitis
- glaucoma

Ask a doctor or pharmacist before use if the child istaking sedatives or tranquilizers

When using this product

- marked drowsiness may occur
- sedatives and tranquilizers may increase drowsiness
- excitability may occur, especially in children

Keep out of reach of children.

In case of overdose, get medical help or contact a Poison Control Center right away 1-800-222-1222

Directions

- find right dose on chart below
- take every 4 to 6 hours, or as directed by a doctor
- do not take more than 6 doses in 24 hours
- mL = milliliter

Age (yr) | Dose (mL)
children under 2 years | do not use
children 2 to 5 years | do not use unless directed by a doctor
children 6 to 11 years | 5 mL to 10 mL

Attention:use only enclosed dosing cup designed for use with this product. Do not use any other dosing device

Other information

- each 5 mL contains: sodium 11 mg
- store at room temperature
- see bottom panel for lot number and expiration date
- protect from light
- contains very low sodium

Inactive ingredients

anhydrous citric acid, carboxymethylcellulose sodium, flavors, glycerin, potassium citrate, purified water, sodium benzoate, sorbitol, sucralose.

Questions?

1-866-467-2748

PRINCIPAL DISPLAY PANEL

Walgreens

NDC 0363-0710-08

Compare to Children’s Benadryl®Dye-Free active ingredient††

children’s ALLERGY Dye-Free Wal-Dryl®

DIPHENHYDRAMINE HCl /ANTIHISTAMINE

12.5 mg/ 5 mL ORAL SOLUTION

DYE & SUGAR FREE

- For the relief of runny nose, itchy throat or nose, sneezing, & itchy, watery eyes
- AGES 6 -11 YEARS

BUBBLE GUM FLAVOR

8 FL OZ (236 mL)

Walgreens

Pharmacist Recommended†

Health expertise you rely on, quality you trust.

†Walgreens Pharmacist Survey

††This product is not manufactured or distributed by Johnson and Johnson owner of the registered trademark Children’s Benadryl®Dye–Free

DO NOT USE IF PRINTED INNER SEAL UNDER CAP IS TORN OR MISSING

IMPORTANT : KEEP THIS CARTON FOR FUTURE REFERENCE ON FULL LABELING

DISTRIBUTED BY: WALGREEN CO.

200 WILMOT RD.,DEERFIELD,IL 60015

Walgreens

100% SATISFACTION GUARANTEED

walgreens.com ©2017 Walgreen Co.